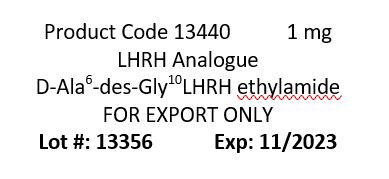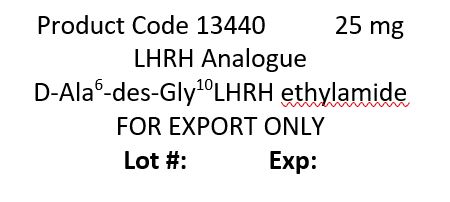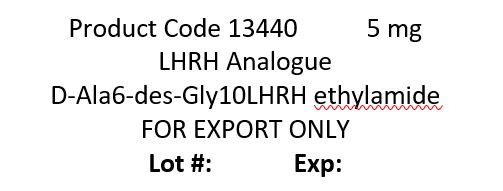 DRUG LABEL: LHRHa
NDC: 50378-018 | Form: INJECTION, POWDER, FOR SUSPENSION
Manufacturer: Western Chemical Inc.
Category: animal | Type: OTC ANIMAL DRUG LABEL
Date: 20230706

ACTIVE INGREDIENTS: ALARELIN ACETATE 800 ug/1 mg

LHRHa
Leutenizing Hormone-Releasing Hormone analogue

WARNING:

Care should be taken to avoid accidental contact or self-injection. In the event of accidental self-injection, seed medical advice immediatley. KEEP OUT OF THE REACH OF CHILDREN

CAUTION:

FOR USE IN BROODSTOCK ONLY

NOT FOR USE IN HUMANS

STORAGE:
Store below 25°C and protect from sunlight. Solutions may be frozen and used at a later date.

DIRECTIONS FOR USE:

LHRHa is packages as a powder ready to be diluted with sterile saline for injection.

LHRHa is a broad species (low specificity) spawning enhancement peptide. The peptide is intended to provide the ability to synchronize spawns and reduce waiting times and spawn failures. Fish must be sexually mature.

CLEANLINESS – Ensure that all equipment is clean, and if possible, sterilized. Always clean equipment with a disinfectant between applications.
INJECTION – Hold the fish firmly and insert the needle into the belly behind the pelvic fin, in the muscle on either side of the dorsal fin or subcutaneously. Inject LHRHa carefully, and quickly remove the needle. Gently place the fish into a container or clean aerated water.
SEDATION FOR HANDLING – If necessary sedate broodstock prior to injection.
RECOVERY – After the fish has recovered from any sedation (5 to 10 minutes), return it to the breeding tank.

DOSE CALCULATION:

The dose calculated based on the weight of the fish. A general dose of LHRHa is 10-20 μg per kilogram of bodyweight. This dose may vary among finfish species and locations. Males may require a reduced dose. Ensure that an adequate ratio of males to females is induced at the same time. For most species a single dose of LHRHa is required. For other species a split dose of one quarter (primer dose) and three quarters (resolving dose) may be required. Environmental and temperature play a significant role in the reproductive process and may affect does and timing.

DILUTION:
Using a sterile syringe and needle, add the appropriate volume of the sterile saline to the LHRHa vial. A volume of 0.1 to 0.5 ml of solution is appropriate for most species. Shake the vial to thoroughly dissolve the LHRHa.
E.g., for 20 fish weighing 5 kg each, use 1 mg vial of LHRHa. Add 10 ml sterile saline to the LHRHa, shake the vial to ensure all of the LHRHa is dissolved. Inject 0.5 ml of solution in each fish.